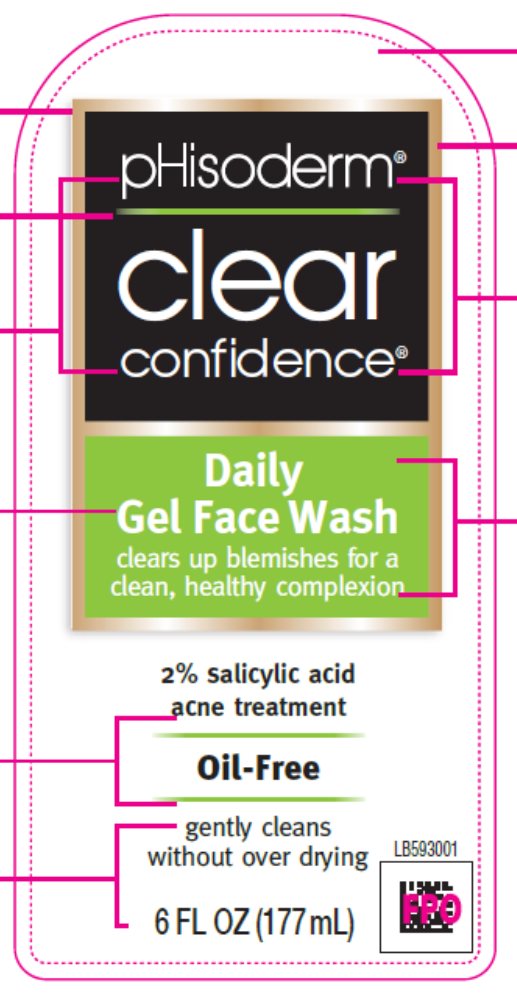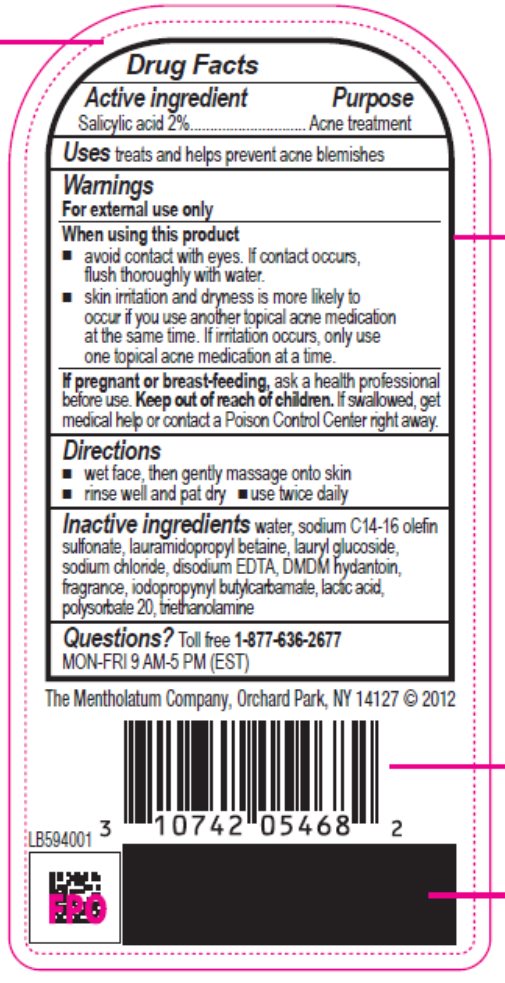 DRUG LABEL: pHisoderm Clear Confidence Daily Gel Face Wash
NDC: 10742-1412 | Form: LIQUID
Manufacturer: The Mentholatum Company
Category: otc | Type: HUMAN OTC DRUG LABEL
Date: 20241213

ACTIVE INGREDIENTS: SALICYLIC ACID 20 mg/1 mL
INACTIVE INGREDIENTS: WATER; SODIUM C14-16 OLEFIN SULFONATE; LAURAMIDOPROPYL BETAINE; LAURYL GLUCOSIDE; SODIUM CHLORIDE; EDETATE DISODIUM; DMDM HYDANTOIN; IODOPROPYNYL BUTYLCARBAMATE; LACTIC ACID, UNSPECIFIED FORM; POLYSORBATE 20; TROLAMINE

Drug Facts - pHisoderm Clear Confidence Daily Gel Face Wash

Active ingredient

Salicylic acid 2%

Purpose

Acne treatment

Uses

treats and helps prevent acne blemishes

Warnings

For external use only

When using this product

- avoid contact with the eyes. If contact occurs, flush thoroughly with water.
- skin irritation and dryness is more likely to occur if you use another topical acne medication at the same time. If irritation occurs, only use one topical acne medication at a time.

If pregnant or breast-feeding

ask a health professional before use.

Keep out of reach of children

If swallowed, get medical help or contact a Poison Control Center right away.

Directions

- wet face, then gently massage onto skin
- rinse well and pat dry
- use twice daily

Inactive ingredients

water, sodium C14-16 olefin sulfonate, lauramidopropyl betaine, lauryl glucoside, sodium chloride, disodium EDTA, DMDM hydantoin, fragrance, iodopropynyl butylcarbamate, lactic acid, polysorbate 20, triethanolamine

Questions?

Toll free 1-877-636-2677 MON-FRI 9 AM-5 PM (EST)